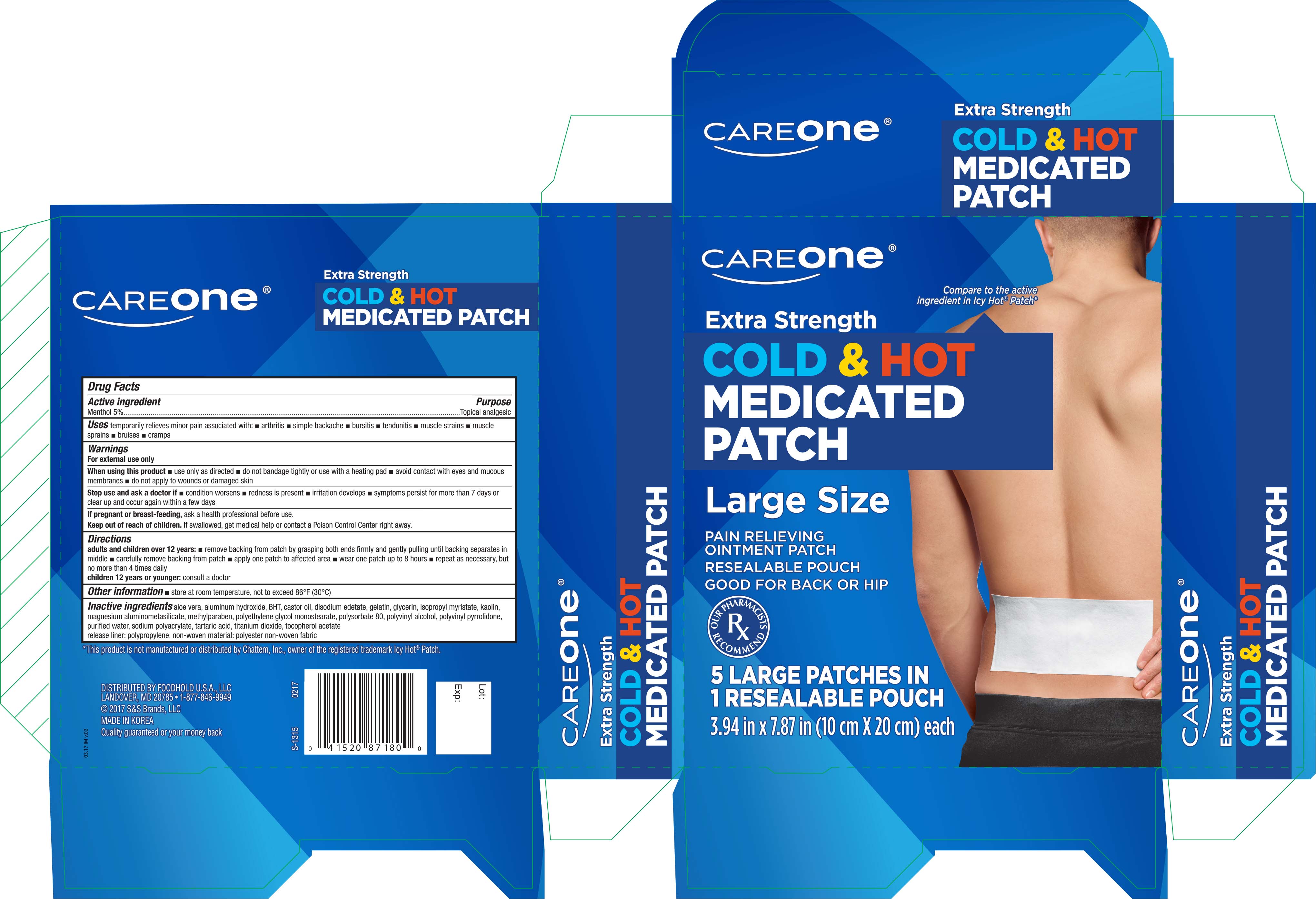 DRUG LABEL: Careone Extra Strength Cold and Hot
NDC: 41520-871 | Form: PATCH
Manufacturer: American Sales Company
Category: otc | Type: HUMAN OTC DRUG LABEL
Date: 20191115

ACTIVE INGREDIENTS: MENTHOL 0.05 mg/1 1
INACTIVE INGREDIENTS: ALOE VERA LEAF; ALUMINUM HYDROXIDE; BUTYLATED HYDROXYTOLUENE; CASTOR OIL; EDETATE DISODIUM; GELATIN; GLYCERIN; ISOPROPYL MYRISTATE; KAOLIN; METHYLPARABEN; POLYSORBATE 80; POLYVINYL ALCOHOL; WATER; SODIUM POLYACRYLATE (8000 MW); TARTARIC ACID; TITANIUM DIOXIDE; .ALPHA.-TOCOPHEROL ACETATE

Active ingredient Purpose

Menthol 5%.................................. Topical analgesic

Uses

Temporarily relieves minor pain associated with:

- arthritis
- simple backache
- bursitis
- tendonitis
- muscle strains
- bruises
- cramps

Warnings

For external use only

When using this product

- use only as directed
- do not bandage tightly or use with a heating pad
- avoid contact with eyes and mucous membranes
- do not apply to wounds or damaged skin

Stop use and ask a doctor if

- condition worsens
- redness is present
- irritation develops
- symptoms persist for more than 7 days or clear up and occur again within a few days

Keep out of reach of children. If swallowed, get medical help or contact a Poision Control Center right away

Directions

adults and children over 12 years:

- remove backing from patch by grasping both ends firmly and gently pulling until backing seperates in middle
- carefully remove backing from patch
- apply one patch to affected area
- wear one patch up to 8 hours
- repeat as necessary, but no more than 4 times daily

children 12 years or younger: consult a doctor

Other information

- store at room temperature, not to exceed 86°F (30°C)

Inactive ingredients

alove vera, aluminum hydroxide, BHT, castor oil, disodium edetate, gelatin, glycerin, isopropyl myristate, kaolin, magnesium aluminometasilicate, methylparaben, polyethylene glycol monostearate, polysorbate 80, polyvinyl alcohol, polyvinyl pyrrolidone, purified water, sodium polyacrylate, tartaric acid, titanium dioxide, tocopherol acetate. Release Liner: polypropylene, non-woven material: polyester non-waven fabric

DOSAGE AND ADMINISTRATION

Distributed by:

Foodhold U.S.A., LLC

Landover, MD 20785

Made in Korea